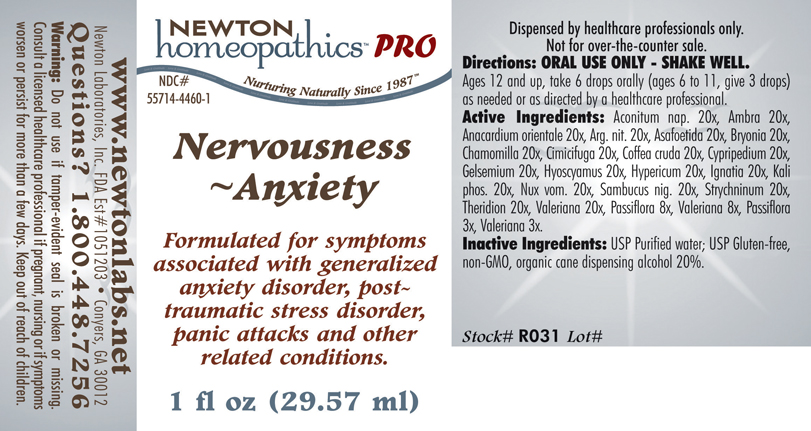 DRUG LABEL: Nervousness - Anxiety 
NDC: 55714-4460 | Form: LIQUID
Manufacturer: Newton Laboratories, Inc.
Category: homeopathic | Type: HUMAN PRESCRIPTION DRUG LABEL
Date: 20110601

ACTIVE INGREDIENTS: Aconitum Napellus 20 [hp_X]/1 mL; Ambergris 20 [hp_X]/1 mL; Semecarpus Anacardium Juice 20 [hp_X]/1 mL; Silver Nitrate 20 [hp_X]/1 mL; Asafetida 20 [hp_X]/1 mL; Bryonia Alba Root 20 [hp_X]/1 mL; Matricaria Recutita 20 [hp_X]/1 mL; Black Cohosh 20 [hp_X]/1 mL; Arabica Coffee Bean 20 [hp_X]/1 mL; Cypripedium Parvifolum Root 20 [hp_X]/1 mL; Gelsemium Sempervirens Root 20 [hp_X]/1 mL; Hyoscyamus Niger 20 [hp_X]/1 mL; Hypericum Perforatum 20 [hp_X]/1 mL; Strychnos Ignatii Seed 20 [hp_X]/1 mL; Potassium Phosphate, Dibasic 20 [hp_X]/1 mL; Strychnos Nux-vomica Seed 20 [hp_X]/1 mL; Sambucus Nigra Flowering Top 20 [hp_X]/1 mL; Strychnine 20 [hp_X]/1 mL; Theridion Curassavicum 20 [hp_X]/1 mL; Valerian 20 [hp_X]/1 mL; Passiflora Incarnata Flowering Top 8 [hp_X]/1 mL
INACTIVE INGREDIENTS: Alcohol

Nervousness - Anxiety

INDICATIONS & USAGE SECTION

Nervousness - Anxiety Formulated for symptoms associated with generalized anxiety disorder, post-traumatic stress disorder, panic attacks and other related conditions.

DOSAGE & ADMINISTRATION SECTION

Directions: ORAL USE ONLY - SHAKE WELL. Ages 12 and up, take 6 drops orally (ages 6 to 11, give 3 drops) as needed or as directed by a healthcare professional.

ACTIVE INGREDIENT SECTION

Aconitum nap. 20x, Ambra 20x, Anacardium orientale 20x, Arg. nit. 20x, Asafoetida 20x, Bryonia 20x, Chamomilla 20x, Cimicifuga 20x, Coffea cruda 20x, Cypripedium 20x, Gelsemium 20x, Hyoscyamus 20x, Hypericum 20x, Ignatia 20x, Kali phos. 20x, Nux vom. 20x, Sambucus nig. 20x, Strychninum 20x, Theridion 20x, Valeriana 20x, Passiflora 8x, Valeriana 8x, Passiflora 3x, Valeriana 3x.

PURPOSE SECTION

Formulated for symptoms associated with generalized anxiety disorder, post-traumatic stress disorder, panic attacks and other related conditions.

INACTIVE INGREDIENT SECTION

Inactive Ingredients: USP Purified water; USP Gluten-free, non-GMO, organic cane dispensing alcohol 20%.

QUESTIONS? SECTION

www.newtonlabs.net Newton Laboratories, Inc. FDA Est # 1051203 - Conyers, GA 30012
Questions? 1.800.448.7256

WARNINGS SECTION

Warning: Do not use if tamper - evident seal is broken or missing. Consult a licensed healthcare professional if pregnant, nursing or if symptoms worsen or persist for more than a few days. Keep out of reach of children.

PREGNANCY OR BREAST FEEDING SECTION

Consult a licensed healthcare professional if pregnant, nursing or if symptoms worsen or persist for more than a few days

KEEP OUT OF REACH OF CHILDREN SECTION

Keep out of reach of children